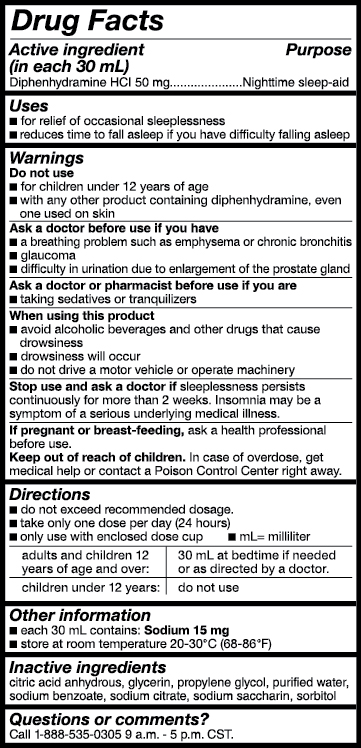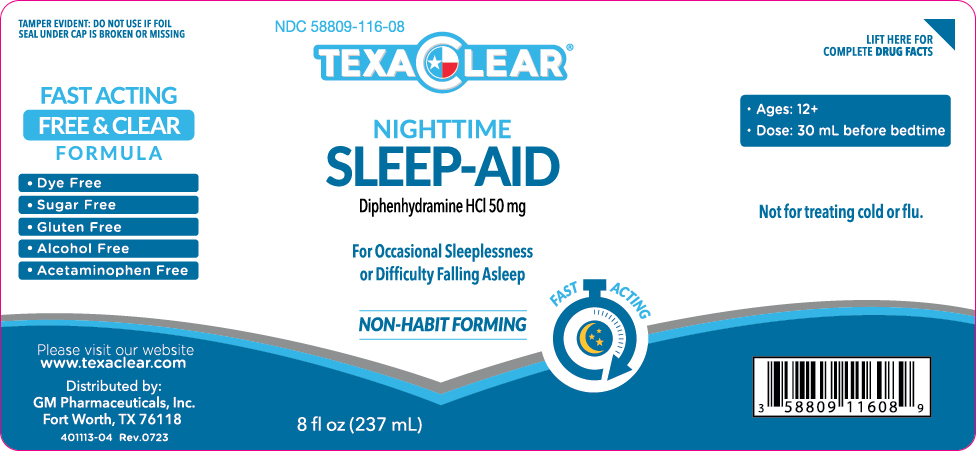 DRUG LABEL: TexaClear Nighttime Sleep-Aid
NDC: 58809-116 | Form: LIQUID
Manufacturer: GM Pharmaceuticals, Inc.
Category: otc | Type: HUMAN OTC DRUG LABEL
Date: 20241007

ACTIVE INGREDIENTS: DIPHENHYDRAMINE HYDROCHLORIDE 50 mg/30 mL
INACTIVE INGREDIENTS: GLYCERIN; SODIUM BENZOATE; SODIUM CITRATE; ANHYDROUS CITRIC ACID; SORBITOL; SACCHARIN SODIUM ANHYDROUS; WATER; PROPYLENE GLYCOL

TexaClear Nighttime Sleep-Aid

Active Ingredients

(in each 30 mL)

Diphenhydramine HCl 50 mg

Purpose

Nighttime Sleep-Aid

Uses

- for the relief of occasional sleeplessnes

- reduces time to fall asleep if you have difficulty falling asleep

Warnings

Do not exceed recommended dosage.

Do not use

- for children under 12 years of age
- with any other product containing diphenhydramine, even one used on skin

Ask a doctor before use if you have

- breathing problems such as emphysema or chronic bronchitis
- glaucoma
- difficulty in urination due to enlargement of the prostate gland

Ask a doctor or pharmacist before use if you are

- taking sedatives or tranquilizers

When using this product

- avoid alcoholic beverages
- drowsiness will occur
- do not drive a motor vehicle or operate machinery

Stop use and ask a doctor if

- sleeplessness persists continuously for more than 2 weeks. Insomnia may be a symptom of serious underlying medical illness.

PREGNANCY OR BREAST FEEDING

If pregnant or breast-feeding,ask a health professional before use.

Directions

- take only 1 dose per day (24-hour period).
- Do not exceed recommended dosage.
- only use with enclosed dose cup
- mL = mililiter

Adults and children 12 years of age and over: | 30 mL at bedtime if needed or as directed by a doctor
Children under12 years of age: | Do not use.

Other Information

- each 30 mL contains: Sodium 15 mg
- store at room temperature 20-30ºC

Inactive ingredients

citric acid anhydrous, glycerin, proplylene glycol, purified water, sodium benzoate, sodium citrate, sodium saccharin, sorbitol

Questions or comments?

Call 1-888-535-0305 9 a.m. - 5 p.m. CST.

KEEP OUT OF REACH OF CHILDREN

In case of overdose, get medical help or contact a Poison Control Center right away.

PACKAGE LABEL

NDC 58809-116-08
TEXACLEAR NIGHTTIME SLEEP-AID
8 fl oz (237mL)